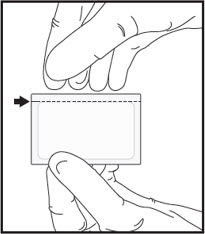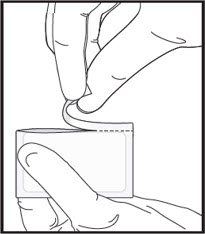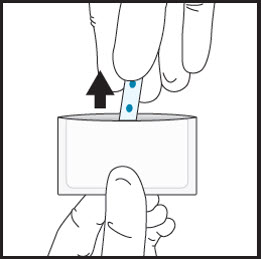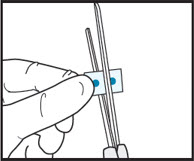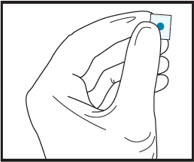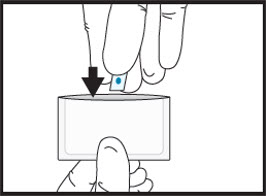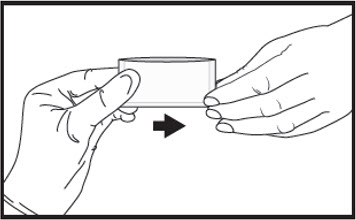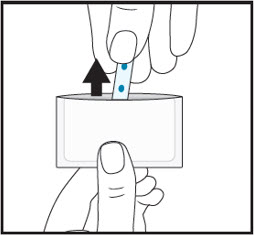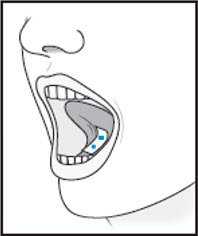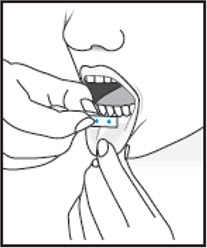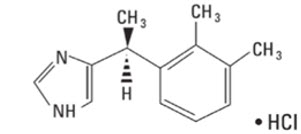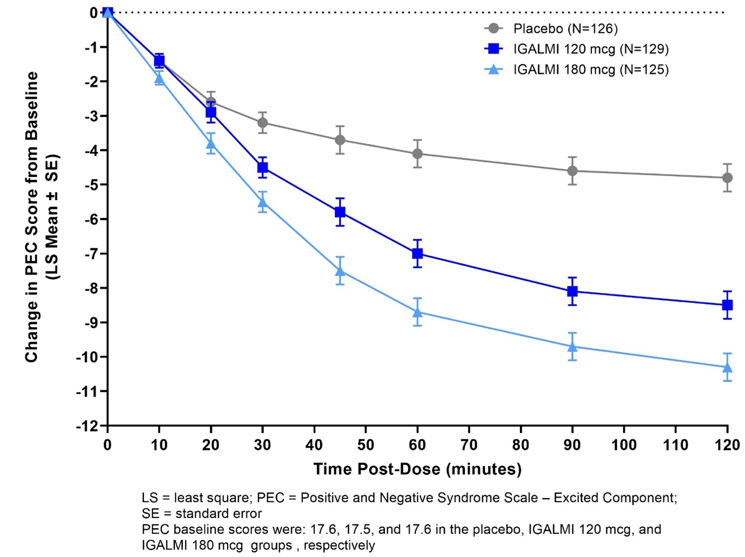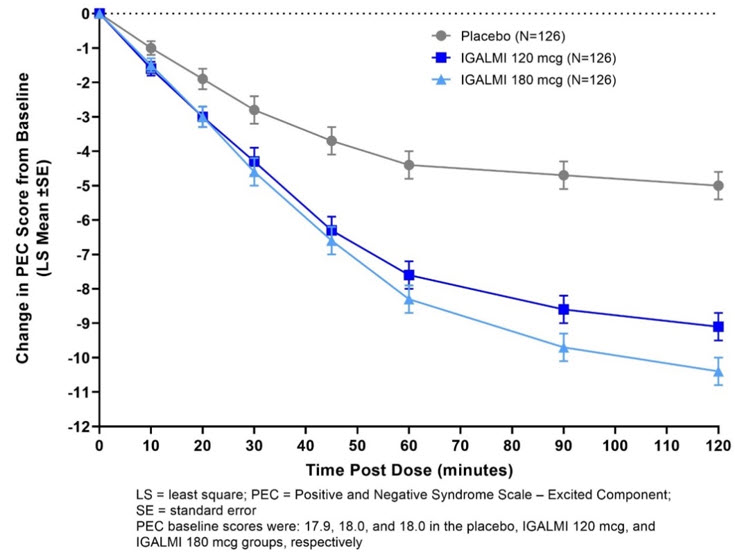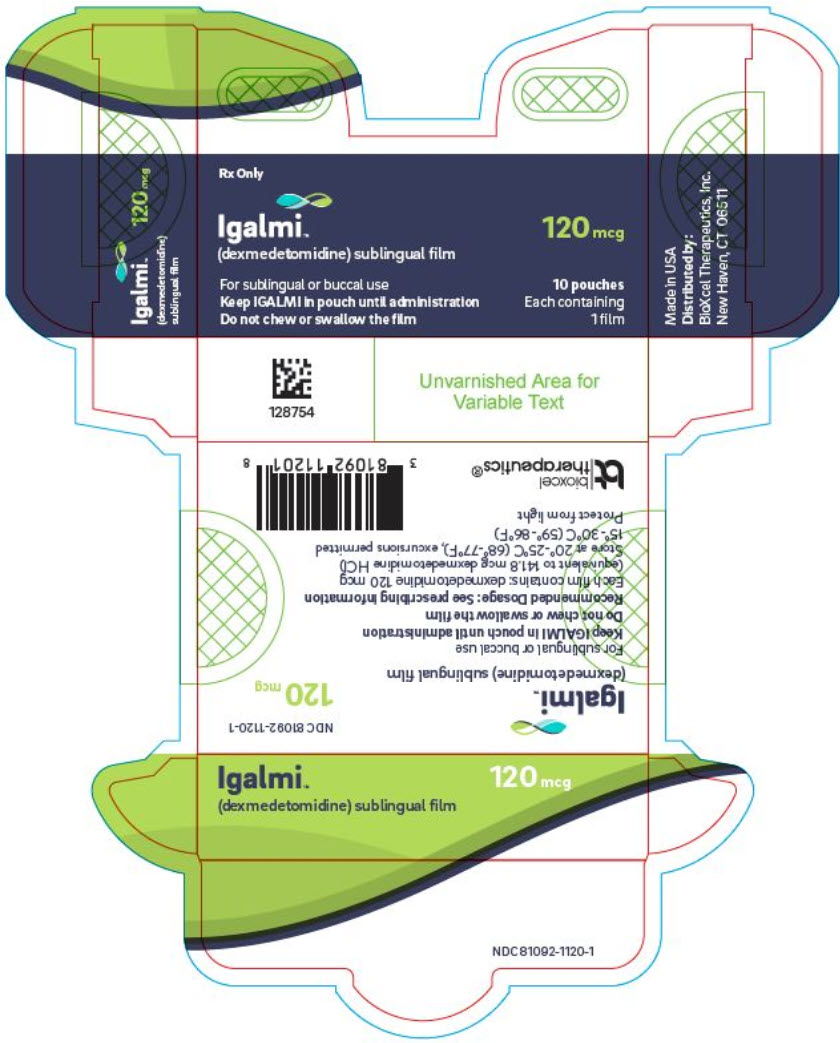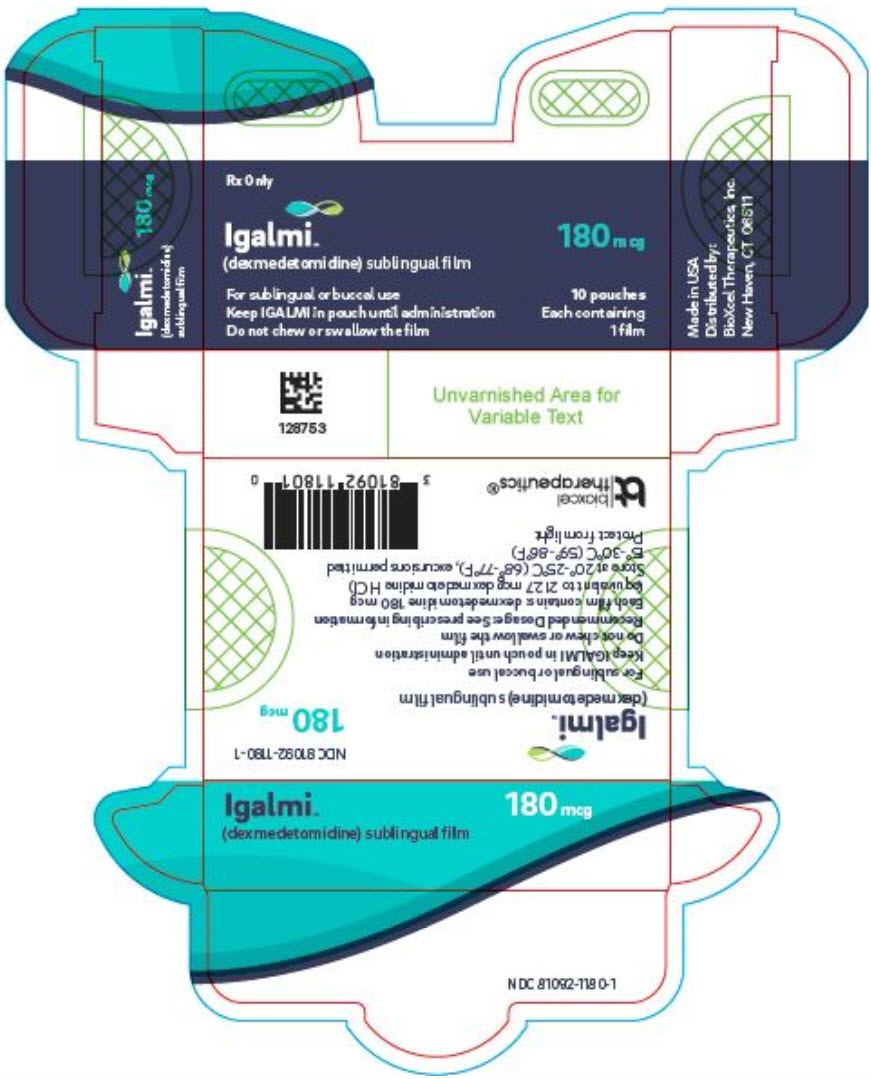 DRUG LABEL: IGALMI
NDC: 81092-1120 | Form: FILM
Manufacturer: BioXcel Therapeutics, Inc.
Category: prescription | Type: HUMAN PRESCRIPTION DRUG LABEL
Date: 20251125

ACTIVE INGREDIENTS: DEXMEDETOMIDINE 120 ug/1 1
INACTIVE INGREDIENTS: POLYETHYLENE GLYCOL, UNSPECIFIED; Sucralose; HYDROXYPROPYL CELLULOSE, UNSPECIFIED; HYDROXYPROPYL CELLULOSE (160000 WAMW); HYDROXYPROPYL CELLULOSE (430000 WAMW); Peppermint Oil; FD&C BLUE NO. 1

HIGHLIGHTS OF PRESCRIBING INFORMATION

These highlights do not include all the information needed to use IGALMI safely and effectively. See full prescribing information for IGALMI.
IGALMI® (dexmedetomidine) sublingual film, for sublingual or buccal use
Initial U.S. Approval: 1999

1 INDICATIONS AND USAGE

IGALMI is an alpha-2 adrenergic receptor agonist indicated in adults for the acute treatment of agitation associated with schizophrenia or bipolar I or II disorder. (1)

Limitations of Use: The safety and effectiveness of IGALMI has not been established beyond 24 hours from the first dose. (1, 5.4, 5.5)

2 DOSAGE AND ADMINISTRATION

- IGALMI should be administered under the supervision of a healthcare provider. A healthcare provider should monitor vital signs and alertness after IGALMI administration to prevent falls and syncope. (2.1)
- Administer sublingually or buccally. Do not chew or swallow. (2.1)
- Recommended dosage (2.2):
  Patient Population | Agitation Severity | Initial Dose [See Full Prescribing Information for recommendations on administering up to two additional doses and maximum recommended dosages.]
  Adults | Mild or Moderate | 120 mcg
  Adults | Severe | 180 mcg
  Mild or Moderate Hepatic Impairment | Mild or Moderate | 90 mcg
  Mild or Moderate Hepatic Impairment | Severe | 120 mcg
  Severe Hepatic Impairment | Mild or Moderate | 60 mcg
  Severe Hepatic Impairment | Severe | 90 mcg
  Geriatric Patients (≥ 65 years old) | Mild, Moderate, or Severe | 120 mcg
- IGALMI 120 mcg and 180 mcg dosage strengths may be cut in half to obtain the 60 mcg and 90 mcg doses, respectively. See Full Prescribing Information for preparation and administration instructions. (2.3)

3 DOSAGE FORMS AND STRENGTHS

Sublingual film: 120 mcg and 180 mcg (3)

4 CONTRAINDICATIONS

None. (4)

5 WARNINGS AND PRECAUTIONS

- Hypotension, Orthostatic Hypotension, and Bradycardia: Avoid use of IGALMI in patients with hypotension, orthostatic hypotension, advanced heart block, severe ventricular dysfunction, or history of syncope. Ensure that patients are alert and not experiencing orthostatic or symptomatic hypotension prior to resuming ambulation. (5.1)
- QT Interval Prolongation: IGALMI prolongs the QT interval; avoid use in patients with risk factors for prolonged QT interval. (5.2)
- Somnolence: Patients should not perform activities requiring mental alertness, such as operating a motor vehicle or operating hazardous machinery for at least eight hours after taking IGALMI. (5.3)

6 ADVERSE REACTIONS

The most common adverse reactions (incidence ≥5% and at least twice the rate of placebo) are somnolence, oral paresthesia or oral hypoesthesia, dizziness, dry mouth, hypotension, and orthostatic hypotension. (6.1)

To report SUSPECTED ADVERSE REACTIONS, contact BioXcel Therapeutics, Inc. at 1-833-201-1088 or FDA at 1-800-FDA-1088 or www.fda.gov/medwatch.

7 DRUG INTERACTIONS

- Drugs that Prolong the QT interval: Avoid use. (7.1)
- Anesthetics, Sedatives, Hypnotics, Opioids: Concomitant use may cause enhanced CNS depressant effects. Reduction in dosage of IGALMI or the concomitant medication may be required. (7.2)

FULL PRESCRIBING INFORMATION

1 INDICATIONS AND USAGE

IGALMI is indicated for the acute treatment of agitation associated with schizophrenia or bipolar I or II disorder in adults.

Limitations of Use

The safety and effectiveness of IGALMI have not been established beyond 24 hours from the first dose [see Warnings and Precautions (5.4, 5.5)].

2 DOSAGE AND ADMINISTRATION

2.1 Important Recommendations Prior to Initiating IGALMI and During Therapy

IGALMI should be administered under the supervision of a healthcare provider. A healthcare provider should monitor vital signs and alertness after IGALMI administration to prevent falls and syncope [see Warnings and Precautions (5.5)].

IGALMI is for sublingual or buccal administration. Do not chew or swallow IGALMI. Do not eat or drink for at least 15 minutes after sublingual administration, or at least one hour after buccal administration.

2.2 Recommended Dosage

Table 1 includes dosage recommendations for IGALMI based on agitation severity for adults, patients with hepatic impairment, and geriatric patients. Lower dosages are recommended for patients with hepatic impairment and geriatric patients [see Warnings and Precautions (5.1) and Use in Specific Populations (8.5, 8.6)].

If agitation persists after the initial dose, up to two additional doses may be administered at least two hours apart. The dosage recommendations for additional doses vary depending upon the patient population and agitation severity (see Table 1). Assess vital signs including orthostatic measurements prior to the administration of any subsequent doses.

Due to risk of hypotension, additional half-doses are not recommended in patients with systolic blood pressure (SBP) less than 90 mmHg, diastolic blood pressure (DBP) less than 60 mmHg, heart rate (HR) less than 60 beats per minute, or postural decrease in SBP ≥ 20 mmHg or in DBP ≥ 10 mmHg.

Table 1: Dosage Recommendations for IGALMI in Adults, Adult Patients with Hepatic Impairment, and Geriatric Patients with Agitation Associated with Schizophrenia or Bipolar I or II Disorder
Patient Population | Agitation Severity | Initial Dose [IGALMI 120 mcg and 180 mcg dosage strengths may be cut in half to obtain the 60 mcg and 90 mcg doses, respectively [see Dosage and Administration (2.3)].] | Optional 2nd/3rd Doses | Maximum Recommended Total Daily Dosage
Adults | Mild or Moderate | 120 mcg | 60 mcg | 240 mcg
Adults | Severe | 180 mcg | 90 mcg | 360 mcg
Patients with Mild or Moderate Hepatic Impairment [Hepatic impairment: Mild (Child-Pugh Class A); Moderate (Child-Pugh Class B); Severe (Child-Pugh Class C)] | Mild or Moderate | 90 mcg | 60 mcg | 210 mcg
Patients with Mild or Moderate Hepatic Impairment [Hepatic impairment: Mild (Child-Pugh Class A); Moderate (Child-Pugh Class B); Severe (Child-Pugh Class C)] | Severe | 120 mcg | 60 mcg | 240 mcg
Patients with Severe Hepatic Impairment | Mild or Moderate | 60 mcg | 60 mcg | 180 mcg
Patients with Severe Hepatic Impairment | Severe | 90 mcg | 60 mcg | 210 mcg
Geriatric Patients (≥ 65 years old) | Mild, Moderate, or Severe | 120 mcg | 60 mcg | 240 mcg

2.3 Preparation and Administration Instructions

Keep IGALMI in the foil pouch until ready to administer. IGALMI should be immediately administered once the pouch is opened and the dose prepared.

Prepare and administer IGALMI under the supervision of a healthcare provider as follows:

Healthcare Professional: Prepare IGALMI Dose for Patient
1 | Open the sealed foil pouch by tearing straight across at the notch.
- Perform Steps 2a, 2b, 2c and 2d only if a 60 mcg or 90 mcg dose (half of a film) is needed, then proceed to Step 3.
- If administering a full dose (1 film), proceed directly to Step 3.
2a | Remove the film from the pouch with clean dry hands.
2b | Cut the film in half between the dots with clean, dry scissors.
2c | Discard unused half in waste container.
2d | Place the half film for administration to the patient back into the pouch.
3 | Immediately give the pouch to the patient.
4 | Instruct patient to remove the film from the pouch with clean dry hands.
5 | For sublingual administration: Instruct patient to place film under the tongue. The film will stick in place. Note: Patient may not eat or drink for 15 minutes after sublingual administration.
5 | For buccal administration: Instruct patient to place film behind lower lip. The film will stick in place. Note: Patient may not eat or drink for one hour after buccal administration.
6 | Instruct patient to:; - Close their mouth. - Allow the film to dissolve. - Do not chew or swallow the film.

3 DOSAGE FORMS AND STRENGTHS

IGALMI is a blue rectangular sublingual film containing on its surface two darker blue spots in dose strengths of 120 mcg and 180 mcg.

4 CONTRAINDICATIONS

None.

5 WARNINGS AND PRECAUTIONS

5.1 Hypotension, Orthostatic Hypotension, and Bradycardia

IGALMI causes dose-dependent hypotension, orthostatic hypotension, and bradycardia. In clinical studies, 18%, 16%, and 9% of patients treated with 180 mcg of IGALMI, 120 mcg of IGALMI, and placebo, respectively, experienced orthostatic hypotension (defined as SBP decrease ≥ 20 mmHg or DBP decrease ≥ 10 mmHg after 1, 3, or 5 minutes of standing) at 2 hours post-dose. In those studies, 7%, 6%, and 1% of patients treated with 180 mcg of IGALMI, 120 mcg of IGALMI, and placebo, respectively, experienced HR ≤ 50 beats per minute within 2 hours of dosing [see Adverse Reactions (6.1)]. In clinical studies with IGALMI, patients were excluded if they had treatment with alpha-1 noradrenergic blockers, benzodiazepines, other hypnotics or antipsychotic drugs four hours prior to study drug administration; had a history of syncope or syncopal attacks; SBP < 110 mmHg; DBP < 70 mmHg; HR < 55 beats per minute; or had evidence of hypovolemia or orthostatic hypotension.

Reports of hypotension and bradycardia, including some resulting in fatalities, have been associated with the use of another dexmedetomidine product given intravenously (IGALMI is for sublingual or buccal use and is not approved for intravenous use). Clinically significant episodes of bradycardia and sinus arrest have been reported after administration of this other dexmedetomidine product to young, healthy adult volunteers with high vagal tone and when this product was given by rapid intravenous or bolus administration.

Because IGALMI decreases sympathetic nervous system activity, hypotension and/or bradycardia may be more pronounced in patients with hypovolemia, diabetes mellitus, or chronic hypertension, and in geriatric patients [see Dosage and Administration (2.2) and Use in Specific Populations (8.5)].

Avoid use of IGALMI in patients with hypotension, orthostatic hypotension, advanced heart block, severe ventricular dysfunction, or history of syncope. After IGALMI administration, patients should be adequately hydrated and should sit or lie down until vital signs are within normal range. If a patient is unable to remain seated or lying down, precautions should be taken to reduce the risk of falls. Ensure that a patient is alert and not experiencing orthostatic hypotension or symptomatic hypotension prior to allowing them to resume ambulation [see Dosage and Administration (2.1)].

5.2 QT Interval Prolongation

IGALMI prolongs the QT interval. Avoid use of IGALMI in patients at risk of torsades de pointes or sudden death including those with known QT prolongation, a history of other arrhythmias, symptomatic bradycardia, hypokalemia or hypomagnesemia, and in patients receiving other drugs known to prolong the QT interval [see Drug Interactions (7.1) and Clinical Pharmacology (12.2)].

5.3 Somnolence

IGALMI can cause somnolence. In placebo-controlled clinical studies in adults with agitation associated with schizophrenia or bipolar I or II disorder, somnolence (including fatigue and sluggishness) was reported in 23% and 22% of patients treated with IGALMI 180 mcg and 120 mcg, respectively, compared to 6% of placebo-treated patients. Patients should not perform activities requiring mental alertness, such as operating a motor vehicle or operating hazardous machinery, for at least eight hours after taking IGALMI [see Adverse Reactions (6.1)].

5.4 Risk of Withdrawal Reactions

Symptoms of withdrawal have been observed after treatment with another dexmedetomidine product administered as a continuous IV infusion in the ICU for another indication. In this study, 12 (5%) adult patients who received intravenous dexmedetomidine up to 7 days (regardless of dose) experienced at least 1 event related to withdrawal within the first 24 hours after discontinuing dexmedetomidine and 7 (3%) adult patients who received intravenous dexmedetomidine experienced at least 1 event related with withdrawal 24 to 48 hours after discontinuing dexmedetomidine. The most common withdrawal reactions were nausea, vomiting, and agitation. In these subjects, tachycardia and hypertension requiring intervention occurred at a frequency of <5% in the 48 hours following intravenous dexmedetomidine discontinuation. Withdrawal symptoms have been reported in pediatric patients who received another dexmedetomidine product intravenously for another indication. IGALMI is not approved for pediatric use.

Withdrawal symptoms reported in published literature include cardiovascular symptoms, such as hypertension, tachycardia, arrhythmias, and in severe cases, hypertensive crisis; neurological symptoms, such as agitation, anxiety, tremors, seizures, and altered mental status; and autonomic symptoms such as diaphoresis, nausea, vomiting, hyperthermia, and mydriasis. In a randomized, double-blind, placebo-controlled, multiple ascending dose study assessing IGALMI at doses up to 120 mcg per day administered over 7 days in healthy volunteers, elevated heart rate and systolic blood pressure and vomiting occurred at a higher frequency upon abrupt discontinuation of 120-mcg doses of IGALMI as compared to placebo. There may be a risk of physical dependence and a withdrawal syndrome if IGALMI is used in a manner other than indicated [see Dosage and Administration (2.2) and Drug Abuse and Dependence (9.3)].

5.5 Tolerance and Tachyphylaxis

Use of another dexmedetomidine product administered intravenously beyond 24 hours has been associated with tolerance and tachyphylaxis and a dose-related increase in adverse reactions. The effectiveness of IGALMI beyond 24 hours after the first dose has not been established. There may be a risk of tolerance and tachyphylaxis if IGALMI is administered at higher doses or for a longer duration than were evaluated, or in a manner other than indicated [see Dosage and Administration (2.2) and Drug Abuse and Dependence (9.3)].

6 ADVERSE REACTIONS

The following adverse reactions are discussed in detail in other sections of the labeling:

- Hypotension, Orthostatic Hypotension, and Bradycardia [see Warnings and Precautions (5.1)]
- QT Interval Prolongation [see Warnings and Precautions (5.2)]
- Somnolence [see Warnings and Precautions (5.3)]
- Risk of Withdrawal Reactions [see Warnings and Precautions (5.4)]
- Tolerance and Tachyphylaxis [see Warnings and Precautions (5.5)]

6.1 Clinical Studies Experience

Because clinical trials are conducted under widely varying conditions, adverse reactions rates observed in the clinical trials of a drug cannot be directly compared to rates in clinical trials of another drug and may not reflect the rates observed in practice.

The safety of IGALMI was evaluated in 507 adult patients with agitation associated with schizophrenia (N=255) or bipolar I or II disorder (N=252) in two randomized, placebo-controlled studies (Studies 1 and 2) [see Clinical Studies (14)]. In both studies, patients were admitted to a clinical research unit or a hospital and remained under medical supervision for at least 24 hours following treatment. Patients were 18 to 71 years of age (mean age was 46 years old); 45% were female and 55% were male; 66% were Black, 31% were White, 2% were multiracial, and 1% were other.

In these studies, patients received an initial dose of IGALMI 180 mcg (N=252), IGALMI 120 mcg (N=255), or placebo (N=252). Patients who were hemodynamically stable (i.e., those with systolic blood pressure (SBP) > 90 mmHg, diastolic blood pressure (DBP) > 60 mmHg, and heart rate (HR) > 60 beats per minute) and without orthostatic hypotension (i.e., reduction in SBP < 20 mmHg or DBP < 10 mmHg upon standing) were eligible for an additional dose after 2 hours. An additional half dose (90 mcg, 60 mcg, or placebo) was given to 7.1% (18/252), 22.7% (58/255) and 44.0% (111/252) of patients in the IGALMI 180 mcg, IGALMI 120 mcg or placebo arms, respectively. After at least an additional 2 hours, an additional second half dose (total IGALMI dose of 360 mcg, total IGALMI dose of 240 mcg, or placebo, respectively) was given to 3.2% (8/252), 9.4% (24/255), and 21.0% (53/252) of patients in the IGALMI 180 mcg, IGALMI 120 mcg or placebo arms, respectively.

In these studies, one patient discontinued treatment due to an adverse reaction of oropharyngeal pain.

The most common adverse reactions (incidence ≥ 5% and at least twice the rate of placebo) were: somnolence, oral paresthesia or oral hypoesthesia, dizziness, dry mouth, hypotension, and orthostatic hypotension.

Table 2 presents the adverse reactions that occurred in IGALMI-treated patients at a rate of at least 2% and at a higher rate than in placebo-treated patients in Studies 1 and 2.

Table 2: Adverse Reactions Reported in ≥2% of IGALMI-Treated Patients and Greater than Placebo in Two Placebo-Controlled Studies of Agitated Adult Patients with Schizophrenia or Bipolar I or II Disorder (Studies 1 and 2)
Adverse Reaction | IGALMI 180 mcg N=252 % | IGALMI 120 mcg N=255 % | Placebo N=252 %
Somnolence [Somnolence includes the terms fatigue and sluggishness] | 23 | 22 | 6
Paresthesia oral or hypoesthesia oral | 7 | 6 | 1
Dizziness | 6 | 4 | 1
Hypotension | 5 | 5 | 0
Orthostatic hypotension | 5 | 3 | <1
Dry mouth | 4 | 7 | 1
Nausea | 3 | 2 | 2
Bradycardia | 2 | 2 | 0
Abdominal discomfort [Abdominal discomfort includes dyspepsia, gastroesophageal reflux disease] | 2 | 0 | 1

Hypotension, Orthostatic Hypotension, and Bradycardia in Two Placebo-Controlled Studies

In clinical studies, patients were excluded if they were treated with alpha-1 noradrenergic blockers, benzodiazepines, antipsychotic drugs, or other hypnotics four hours prior to study drug administration; had a history of syncope or syncopal attacks; their SBP was less than 110 mmHg; their DBP was less than 70 mmHg; their HR was less than 55 beats per minute; or they had evidence of hypovolemia or orthostatic hypotension. In these studies, vital signs were monitored (at 30 minutes, 1-, 2-, 4-, 6-, and 8-hours post-dose), including orthostatic vital signs at 2-, 4-, and 8-hours post-dose. Maximum positional decreases in SBP and DBP after standing were observed at two hours post-dose. Maximal reductions on BP and HR were observed two hours post-dose.

Table 3 presents the mean BP and HR decrease across all patients from both studies at 2 hours post dose.

Table 3: Mean Blood Pressure and Heart Rate Decrease At 2 Hours Post-Dose
 | IGALMI 180 mcg N=252 | IGALMI 120 mcg N=255 | Placebo N=252
Mean SBP Decrease (mmHg) | 15 | 13 | 1
Mean DBP Decrease (mmHg) | 8 | 7 | <1
Mean Heart Rate Decrease (bpm) | 9 | 7 | 3

In the clinical studies:

- 13%, 8%, and < 1% of patients in the single dose 180 mcg IGALMI, 120 mcg IGALMI, and placebo groups, respectively, experienced SBP ≤ 90 mmHg and a decrease ≥ 20 mmHg of SBP within 24 hours of dosing.
- 19%, 17%, and 2% of the patients in the 180 mcg IGALMI, 120 mcg IGALMI, and placebo groups, respectively, had a DBP ≤ 60 mmHg and a DBP decrease ≥ 10 mmHg within 24 hours of dosing.
- 4%, 3%, and 0% of patients in the 180 mcg IGALMI, 120 mcg IGALMI, and placebo groups, respectively, had a HR ≤ 50 beats per minute and a HR decrease ≥ 20 beats per minute within 24 hours of dosing.

At 8 hours post-dose, 2% of patients in the IGALMI 180 mcg group experienced a SBP ≤ 90 mmHg and decrease ≥ 20 mmHg compared with one patient (<1%) in the IGALMI 120 mcg group and none in the placebo group. At 24 hours, none of the patients in the IGALMI 180 mcg group experienced a SBP ≤90 mmHg and decrease ≥ 20 mmHg compared with one patient (<1%) in the IGALMI 120 mcg group and none in the placebo group. At 8 hours post-dose, none of the patients in the IGALMI 180 mcg group had a HR ≤ 50 beats per minute and a HR decrease ≥ 20 beats per minute compared with one patient in the 120 mcg group (<1%) and none in the placebo group.

6.2 Postmarketing Experience

The following adverse reactions have been identified during post approval use of another dexmedetomidine product given intravenously (IGALMI is not approved for intravenous use). Because these reactions are reported voluntarily from a population of uncertain size, it is not always possible to reliably estimate their frequency or establish a causal relationship to drug exposure.

- Blood and Lymphatic System Disorders: Anemia
- Cardiac Disorders: Arrhythmia, atrial fibrillation, atrioventricular block, bradycardia, cardiac arrest, cardiac disorder, extrasystoles, myocardial infarction, supraventricular tachycardia, tachycardia, ventricular arrhythmia, ventricular tachycardia
- Eye Disorders: Photopsia, visual impairment
- Gastrointestinal Disorders: Abdominal pain, diarrhea, nausea, vomiting
- General Disorders and Administration Site Conditions: Chills, hyperpyrexia, pain, pyrexia, thirst
- Hepatobiliary Disorders: Hepatic function abnormal, hyperbilirubinemia
- Investigations: Alanine aminotransferase increased, aspartate aminotransferase increased, blood alkaline phosphatase increased, blood urea increased, electrocardiogram T wave inversion, gammaglutamyltransferase increased, electrocardiogram QT prolonged
- Metabolism and Nutrition Disorders: Acidosis, hyperkalemia, hypoglycemia, hypovolemia, hypernatremia
- Nervous System Disorders: Convulsion, dizziness, headache, neuralgia, neuritis, speech disorder
- Psychiatric Disorders: Agitation, confusional state, delirium, hallucination, illusion
- Renal and Urinary Disorders: Oliguria, polyuria
- Respiratory, Thoracic and Mediastinal Disorders: Apnea, bronchospasm, dyspnea, hypercapnia, hypoventilation, hypoxia, pulmonary congestion, respiratory acidosis
- Skin and Subcutaneous Tissue Disorders: Hyperhidrosis, pruritus, rash, urticaria
- Surgical and Medical Procedures: Light anesthesia
- Vascular Disorders: Blood pressure fluctuation, hemorrhage, hypertension, hypotension

7 DRUG INTERACTIONS

7.1 Drugs that Prolong the QT Interval

Concomitant use of drugs that prolong the QT interval may add to the QT-prolonging effects of IGALMI and increase the risk of cardiac arrhythmia. Avoid the use of IGALMI in combination with other drugs known to prolong the QT interval [see Warnings and Precautions (5.2)].

7.2 Anesthetics, Sedatives, Hypnotics, and Opioids

Concomitant use of IGALMI with anesthetics, sedatives, hypnotics, or opioids is likely to lead to enhanced CNS depressant effects. Specific studies with another dexmedetomidine product given intravenously have confirmed these effects with sevoflurane, isoflurane, propofol, alfentanil, and midazolam. Due to possible enhanced CNS effects when given concomitantly with IGALMI, consider a reduction in dosage of IGALMI or the concomitant anesthetic, sedative, hypnotic, or opioid.

8 USE IN SPECIFIC POPULATIONS

8.1 Pregnancy

Risk Summary

There are no available data on IGALMI use in pregnant women to evaluate for a drug-associated risk of major birth defects, miscarriage or other adverse maternal or fetal effects. Available data from published randomized controlled trials and case reports over several decades of use with intravenously administered dexmedetomidine during pregnancy have not identified a drug-associated risk of major birth defects or miscarriage; however, the reported exposures occurred after the first trimester. Most of the available data are based on studies with exposures that occurred at the time of cesarean-section delivery, and these studies have not identified an adverse effect on maternal outcomes or infant Apgar scores. Available data indicate that dexmedetomidine crosses the placenta.

In animal reproductive studies fetal toxicity occurred in the presence of maternal toxicity with subcutaneous administration of dexmedetomidine to pregnant rats during organogenesis at doses 5 times the maximum recommended human dose [MRHD] of 360 mcg/day based on mg/m^2 body surface area. Adverse developmental effects, including early implantation loss and decreased viability of second generation offspring, occurred when pregnant rats were subcutaneously administered doses less than or equal to the MRHD based on mg/m^2 from late pregnancy through lactation and weaning (see Data).

The estimated background risk of major birth defects and miscarriage for the indicated population is unknown. All pregnancies have a background risk of birth defect, loss, or other adverse outcomes. In the U.S. general population, the estimated background risk of major birth defects and miscarriage in clinically recognized pregnancies is 2 to 4% and 15 to 20%, respectively.

Data

Animal Data

Increased post-implantation losses and reduced live pups in the presence of maternal toxicity (decreased body weight) occurred in a rat embryo-fetal development study in which pregnant dams were administered subcutaneous doses of dexmedetomidine of 200 mcg/kg/day (equivalent to 5 times the MRHD of 360 mcg/day based on mg/m^2) during the period of organogenesis (Gestation Day (GD) 5 to 16). No embryo-fetal toxicity was observed at 20 mcg/kg/day (less than the MRHD of 360 mcg/day based on mg/m^2). No malformations were reported at any dose level.

No malformation or embryo-fetal toxicity were observed in a rabbit embryo-fetal developmental study in which pregnant dams were administered dexmedetomidine intravenously at doses up to 96 mcg/kg/day (equivalent to 5 times the MRHD of 360 mcg/day based on mg/m^2) during the period of organogenesis (GD 6 to 18).

Reduced pup and adult offspring weights and grip strength were reported in a rat developmental toxicology study in which pregnant females were administered dexmedetomidine subcutaneously at 8 mcg/kg/day (less than the MRHD of 360 mcg/day based on mg/m^2) during late pregnancy through lactation and weaning (GD 16 to postnatal day [PND] 25). Decreased viability of second generation offspring and an increase in early implantation loss along with delayed motor development occurred at 32 mcg/kg/day (equivalent to the MRHD of 360 mcg/day based on mg/m^2) when first generation offspring were mated. This study limited dosing to hard palate closure (GD 15-18) through weaning instead of standard dosing from implantation (GD 6-7) to weaning (PND 21).

8.2 Lactation

Risk Summary

Available published literature report the presence of dexmedetomidine in human milk following intravenous administration. There is no information regarding the effects of dexmedetomidine on the breastfed child or the effects on milk production. Advise women to monitor the breastfed infant for irritability. The developmental and health benefits of breastfeeding should be considered along with the mother's clinical need for IGALMI and any potential adverse effects on the breastfed child from IGALMI or from the underlying maternal condition.

8.4 Pediatric Use

The safety and effectiveness of IGALMI have not been established in pediatric patients.

8.5 Geriatric Use

Fifteen geriatric patients (≥ 65 years of age) were enrolled (no patients were 75 years of age and older) in the clinical studies for acute treatment of agitation associated with schizophrenia or bipolar I or II disorder. Of the total number of IGALMI-treated patients in these clinical studies, 11/507 (2.2%) were 65 years of age and older [see Clinical Studies (14)].

Dosage reduction of IGALMI is recommended in geriatric patients [see Dosage and Administration (2.2)]. A higher incidence of bradycardia and hypotension was observed in geriatric patients compared to younger adult patients after intravenous administration of another dexmedetomidine product [see Warnings and Precautions (5.1)]. The pharmacokinetic profile of intravenous dexmedetomidine was not altered in geriatric subjects [see Clinical Pharmacology (12.3)].

Clinical studies of IGALMI did not include sufficient numbers of patients 65 years of age and older to determine whether there were differences in the effectiveness of IGALMI in the acute treatment of agitation associated with schizophrenia or bipolar I or II disorder compared to younger adult patients.

8.6 Hepatic Impairment

Dexmedetomidine clearance was decreased in patients with hepatic impairment (Child-Pugh Class A, B, or C). Thus, a dosage reduction of IGALMI is recommended in patients with hepatic impairment compared to patients with normal hepatic function [see Dosage and Administration (2.2) and Clinical Pharmacology (12.3)].

9 DRUG ABUSE AND DEPENDENCE

9.1 Controlled Substance

IGALMI contains dexmedetomidine, which is not a controlled substance.

9.3 Dependence

Physical Dependence

Dexmedetomidine is an alpha-2 adrenergic agonist and has been associated with physical dependence, as manifested by a withdrawal syndrome with abrupt drug discontinuation, particularly after prolonged continuous intravenous use in critical care settings. Physical dependence is a state that develops as a result of physiological adaptation in response to repeated drug use, manifested by withdrawal signs and symptoms after abrupt discontinuation or a significant dose reduction of a drug. Withdrawal signs and symptoms associated with physical dependence produced by dexmedetomidine, as reported in the literature, include cardiovascular findings, such as hypertension, tachycardia, arrhythmias, and in severe cases, hypertensive crisis; neurological findings, such as agitation, anxiety, tremors, seizures, and altered mental status; and autonomic findings, such as diaphoresis, nausea, vomiting, hyperthermia, and mydriasis.

The potential for IGALMI to produce a withdrawal syndrome was evaluated in two clinical studies. The first was a single-arm, open-label clinical study that evaluated adult patients diagnosed with agitation associated with schizophrenia or bipolar disorder after a 7-day IGALMI treatment period. This study demonstrated that, with a mean of 3 doses (min, max: 1, 7; SD: 1.69) administered in the 7-day treatment period and with no patient receiving more than a single 180 mcg daily dose, there was no evidence of dexmedetomidine withdrawal signs or symptoms.

The second was a randomized, double-blind, placebo-controlled, multiple ascending dose study conducted in healthy volunteers that assessed IGALMI 30 to 120 mcg daily administered over 7 days. The findings from this study are suggestive of dexmedetomidine withdrawal symptoms (e.g., increased heart rate and systolic blood pressure, vomiting) upon abrupt discontinuation with the hemodynamic changes being more frequently reported in the 120-mcg single daily dose group as compared to [see Dosage and Administration (2.1, 2.2) and Warnings and Precautions (5.4)].

Tolerance

Tolerance is a physiological state characterized by a reduced response to a drug after repeated administration (i.e., a higher dose of a drug is required to produce the same effect that was once obtained at a lower dose).

-There may be a risk for tolerance if IGALMI is administered in a manner other than indicated [see Dosage and Administration (2.1, 2.2) and Warnings and Precautions (5.5)].

10 OVERDOSAGE

In a tolerability study of intravenous dexmedetomidine in which healthy adult subjects were administered doses at and above the recommended dose of 0.2 to 0.7 mcg/kg/hour, the maximum blood concentration was approximately 13 times the upper boundary of the therapeutic range for the intravenous dexmedetomidine (IGALMI is not approved for intravenous use). The most notable effects observed in two subjects who achieved the highest doses were first degree atrioventricular block and second-degree heart block.

Five adult patients received an overdose of intravenous dexmedetomidine in intensive care unit sedation studies. Two patients who received a 2 mcg/kg loading dose (twice the recommended loading dose) over 10 minutes, experienced bradycardia and/or hypotension.

One patient who received a loading intravenous bolus dose of undiluted dexmedetomidine (19.4 mcg/kg), had cardiac arrest from which he was successfully resuscitated.

Consider contacting a Poison Center (1-800-222-1222) or a medical toxicologist for overdosage management recommendations for IGALMI.

11 DESCRIPTION

IGALMI contains dexmedetomidine, an alpha-2 adrenergic receptor agonist, present as dexmedetomidine hydrochloride, the S-enantiomer of medetomidine chemically described as 4-[(1S)-1- (2, 3-dimethylphenyl) ethyl]-1H-imidazole hydrochloride. The empirical formula is C13H16N2∙HCl with a molecular weight of 236.7 g/mol. The structural formula of dexmedetomidine hydrochloride is:

Dexmedetomidine hydrochloride is a white or almost white powder that is freely soluble in water and has a pKa of 7.1. Its partition coefficient in octanol/water at pH 7.4 is 2.89.

IGALMI is for sublingual or buccal use. Each IGALMI sublingual film contains 120 mcg or 180 mcg of dexmedetomidine equivalent to 141.8 mcg and 212.7 mcg of dexmedetomidine hydrochloride, respectively.

IGALMI contains the following inactive ingredients: FD&C Blue #1 colorant, hydroxypropyl cellulose, peppermint oil, polyethylene oxide, and sucralose.

12 CLINICAL PHARMACOLOGY

12.1 Mechanism of Action

Dexmedetomidine is an alpha-2 adrenergic receptor agonist. The mechanism of action of IGALMI in the acute treatment of agitation associated with schizophrenia or bipolar I or II disorder is thought to be due to activation of presynaptic alpha-2 adrenergic receptors.

12.2 Pharmacodynamics

Dexmedetomidine acts as an agonist at alpha-2 adrenergic receptors with binding affinities (Ki values) of 4 to 6 nM at the alpha-2 adrenergic receptor subtypes.

Cardiac Electrophysiology

IGALMI exhibits a concentration dependent QT prolongation. Table 4 shows the mean (upper 90% confidence interval) QTcF increase from baseline for respective dosing regimens [see Warnings and Precautions (5.2)].

Table 4: QTcF Increase from Baseline by Dosage of IGALMI
IGALMI Dosage | Mean QTcF Increase from Baseline (upper 90% confidence interval)
120 mcg single use | 6 (7) msec
120 mcg + 2 additional doses of 60 mcg 2 hours apart (total 3 doses) | 8 (9) msec
180 mcg single use | 8 (11) msec
180 mcg + 2 additional doses of 90 mcg 2 hours apart (total 3 doses) | 11 (14) msec

12.3 Pharmacokinetics

Dexmedetomidine exposure (Cmax and AUC) increased in a dose proportional manner in the dose range of 20 mcg (0.17 times the lowest recommended initial dose of 120 mcg) to 180 mcg after single sublingual administration of IGALMI.

The mean time for film to dissolve in the mouth was about 6 to 8 minutes and 18 minutes following sublingual and buccal administration, respectively. Dexmedetomidine was quantifiable in plasma generally after 5 to 20 minutes post dosing.

Absorption

The absolute bioavailability of dexmedetomidine was about 72% and 82% following sublingual and buccal administration of IGALMI, respectively. When water was taken at two hours post dose, comparable exposures of dexmedetomidine were observed when IGALMI was administered by both routes.

Mean maximal plasma concentrations of dexmedetomidine were reached approximately two hours after sublingual or buccal administration of IGALMI. Following sublingual administration of 40 mcg of IGALMI (0.33 times the lowest recommended initial dose) with water drinking at two hours post dose and 20 mcg dexmedetomidine intravenous infusion for 90 minutes in healthy volunteers:

- The mean peak plasma concentration (Cmax) of dexmedetomidine was 143 ng/L and 144 ng/L, respectively.
- The mean area under concentration curve (AUC) of dexmedetomidine was 851 hour*ng/L and 584 hour*ng/L, respectively.

Effect of Drinking Water on Absorption

Compared to drinking water at two hours post sublingual administration of IGALMI, early water intake (as early as 15 minutes post dose) had minimal effects on the rate or extent of absorption of dexmedetomidine.

Effects of early water intake (i.e., before two hours post dose) on the absorption of dexmedetomidine has not been evaluated following buccal administration.

Distribution

The steady-state volume of distribution (Vss) of dexmedetomidine following intravenous administration was approximately 118 liters. Dexmedetomidine protein binding was assessed in the plasma of healthy male and female subjects. The average protein binding was 94% and was constant across the different plasma concentrations tested. Protein binding was similar in males and females. The fraction of dexmedetomidine that was bound to plasma proteins was significantly decreased in subjects with hepatic impairment compared to healthy subjects.

The potential for protein binding displacement of dexmedetomidine by fentanyl, ketorolac, theophylline, digoxin and lidocaine was explored in vitro, and negligible changes in the plasma protein binding of dexmedetomidine IV were observed. The potential for protein binding displacement of phenytoin, warfarin, ibuprofen, propranolol, theophylline and digoxin by dexmedetomidine hydrochloride injection was explored in vitro and none of these compounds appeared to be significantly displaced by intravenous dexmedetomidine.

Elimination

Metabolism

Dexmedetomidine undergoes almost complete biotransformation with very little unchanged dexmedetomidine excreted in urine and feces. Biotransformation involves both direct glucuronidation as well as cytochrome P450 mediated metabolism. The major metabolic pathways of dexmedetomidine are: direct N-glucuronidation to inactive metabolites; aliphatic hydroxylation (mediated primarily by CYP2A6 with a minor role of CYP1A2, CYP2E1, CYP2D6 and CYP2C19) of dexmedetomidine to generate 3-hydroxy-dexmedetomidine, the glucuronide of 3-hydroxy-dexmedetomidine, and 3-carboxy-dexmedetomidine; and N-methylation of dexmedetomidine to generate 3-hydroxy N-methyl-dexmedetomidine, 3-carboxy N-methyl-dexmedetomidine, and dexmedetomidine-N-methyl O-glucuronide.

Excretion

The mean terminal elimination half-life (t1/2) of dexmedetomidine is approximately 2.8 hours following sublingual or buccal administration of IGALMI. Clearance is estimated to be approximately 39 L/h following intravenous administration.

A mass balance study demonstrated that after nine days, an average of 95% of the radioactivity, following intravenous administration of radiolabeled dexmedetomidine, was recovered in the urine and 4% in the feces. No unchanged dexmedetomidine was detected in the urine. Approximately 85% of the radioactivity recovered in the urine was excreted within 24 hours after the infusion. Fractionation of the radioactivity excreted in urine demonstrated that products of N-glucuronidation accounted for approximately 34% of the cumulative urinary excretion. In addition, aliphatic hydroxylation of parent drug to form 3-hydroxy-dexmedetomidine, the glucuronide of 3-hydroxy-dexmedetomidine, and 3-carboxylic acid-dexmedetomidine together represented approximately 14% of the dose in urine. N-methylation of dexmedetomidine to form 3-hydroxy N-methyl dexmedetomidine, 3-carboxy N-methyl dexmedetomidine, and N-methyl O-glucuronide dexmedetomidine accounted for approximately 18% of the dose in urine. The N-methyl metabolite itself was a minor circulating component and was undetected in urine. Approximately 28% of the urinary metabolites have not been identified.

Specific Populations

Male and Female Patients

There was no observed difference in the pharmacokinetics of intravenous dexmedetomidine due to sex.

Geriatric Patients

The pharmacokinetic profile of intravenous dexmedetomidine was not altered by age. There were no differences in the pharmacokinetics of intravenous dexmedetomidine in young (18–40 years), middle age (41–65 years), and geriatric (>65 years) subjects.

Patients with Hepatic Impairment

In subjects with varying degrees of hepatic impairment (Child-Pugh Class A, B, or C), clearance values for intravenous dexmedetomidine were lower than in subjects with normal hepatic function [see Dosage and Administration (2.2)]. After an intravenous infusion of 0.6 mcg/kg of this dexmedetomidine product over 10 minutes the mean clearance values for subjects with mild, moderate, and severe hepatic impairment were 74%, 64% and 53% of those observed in subjects with normal hepatic function, respectively. Mean clearances for free drug were 59%, 51% and 32% of those observed in subjects with normal hepatic function, respectively.

Patients with Renal Impairment

Dexmedetomidine pharmacokinetics (Cmax, Tmax, AUC, t1/2, CL, and V) were not significantly different in patients with creatinine clearance <30 mL/minute compared to subjects with normal renal function.

Drug Interactions Studies

In vitro studies in human liver microsomes demonstrated no evidence of cytochrome P450 mediated drug interactions that are likely to be of clinical relevance.

13 NONCLINICAL TOXICOLOGY

13.1 Carcinogenesis, Mutagenesis, Impairment of Fertility

Carcinogenesis

Animal carcinogenicity studies have not been performed with dexmedetomidine.

Mutagenesis

Dexmedetomidine was not mutagenic in the in vitro Ames bacterial reverse mutation test or mammalian mouse lymphoma cell forward mutation assay. Dexmedetomidine was not clastogenic in the in vitro human lymphocyte chromosome aberration test in the absence or presence of human liver S9 metabolic activation, however, a weak clastogenic response was noted in the presence of rat liver S9 metabolic activation. Dexmedetomidine was not clastogenic in the in vivo bone marrow micronucleus test in CD-1 mice, although there was some evidence for clastogenicity in NMRI mice.

Impairment of Fertility

Fertility in male or female rats was not affected after daily subcutaneous injections of dexmedetomidine at doses up to 54 mcg/kg (1.5 times the MRHD of 360 mcg/day on a mg/m^2 basis) administered from 10 weeks prior to mating in males, and 3 weeks prior to mating and during mating in females.

13.2 Animal Toxicology and/or Pharmacology

Twice daily sublingual administration of 120 to 320 mcg/day of dexmedetomidine to dogs for 28 days caused decreased heart rate and moderate sedation up to 3.5 hours post dose. A single male dog (out of 32 treated dogs) dosed 320 mcg/day (equivalent to the MRHD of 360 mcg/day) exhibited inflammation, necrosis, myofiber degeneration, and hemorrhage at the sublingual treatment site. No adverse effects were noted at 240 mcg/day (less than the MRHD of 360 mcg/day).

14 CLINICAL STUDIES

The effectiveness of IGALMI for the acute treatment of agitation associated with schizophrenia or bipolar I or II disorder in adults was established in two randomized, double-blind, placebo-controlled, fixed-dose studies (Studies 1 and 2):

- Study 1 (NCT04268303) included 380 patients who met DSM-5 criteria for schizophrenia, schizoaffective or schizophreniform disorder. The population was 18 to 71 years of age (mean age was 46 years old); 37% female and 63% male; 78% Black, 20% White, 1% multiracial, and 1% Asian.
- Study 2 (NCT04276883) included 378 patients who met DSM-5 criteria for bipolar I or II disorder. The population was 18 to 70 years of age (mean age was 47 years old); 55% female and 45% male; 56% Black, 41% White, 1% Asian, 1% multiracial, and 1% other.

The Positive and Negative Syndrome Scale-Excited Component (PEC) is an investigator-rated instrument consisting of 5 items: poor impulse control, tension, hostility, uncooperativeness, and excitement. Each item is scored on a scale from 1 to 7 (1=absent, 2=minimal, 3=mild, 4=moderate, 5=moderate-severe, 6=severe, 7=extremely severe). The total PEC score ranges from 5 to 35, with higher scores reflecting greater overall symptom severity. For enrollment in the studies, patients had to be judged to be clinically agitated with a total PEC score of ≥ 14, with at least one individual item score ≥ 4. In both studies, patients were admitted to a clinical research unit or a hospital and remained under medical supervision for at least 24 hours following treatment.

Patients were randomized to receive a single sublingual dose of 180 mcg of IGALMI, 120 mcg of IGALMI, or placebo. The primary efficacy endpoint in both studies was the change from baseline in the PEC score, assessed two hours following the initial dose. The key secondary endpoint was the time to effect onset, assessed by measuring the change from baseline in PEC score at 10, 20, 30, 45, 60, and 90 minutes after the initial dose administration.

In both studies, mean baseline PEC scores were similar in all treatment groups (Table 5). The mean change from baseline in the PEC total score at two hours after the first dose in patients treated with 180 mcg and 120 mcg of IGALMI was statistically greater than patients who received placebo (Table 5).

Examination of population subsets (race and sex) on the primary endpoint did not show evidence for differential responsiveness between White and Black or female and male patients. The clinical studies did not include enough patients of other races or patients ≥65 years of age to determine whether there were differences in effectiveness for those groups.

Table 5: Primary Efficacy Results for Change from Baseline in the PEC Score at Two Hours in Agitated Patients with Schizophrenia or Bipolar I or II Disorder (Studies 1 and 2)
Study | Treatment Group | Number of Patients | Mean Baseline PEC Score (SD) | LS Mean Change from Baseline to 2 hour Post First Dose (SE) | LS Mean Difference (95% CI)
Study 1 | IGALMI 180 mcg [IGALMI doses that were statistically significantly superior to placebo after adjusting for multiplicity.] | 125 | 17.6 (2.7) | -10.3 (0.4) | -5.5 (-6.5, -4.4)
Study 1 | IGALMI 120 mcg | 129 | 17.5 (2.5) | -8.5 (0.4) | -3.7 (-4.8, -2.7)
Study 1 | Placebo | 126 | 17.6 (2.3) | -4.8 (0.4) | -
Study 2 | IGALMI 180 mcg | 126 | 18.0 (3.0) | -10.4 (0.4) | -5.4 (-6.5, -4.3)
Study 2 | IGALMI 120 mcg | 126 | 18.0 (2.7) | -9.1 (0.4) | -4.1 (-5.1, -3.0)
Study 2 | Placebo | 126 | 17.9 (2.9) | -5.0 (0.4) | -
SD=standard deviation; SE=standard error; LS Mean=least-squares mean; CI=unadjusted confidence interval; PEC=Positive and Negative Syndrome Scale-Excited Component

Figures 1 and 2 show the changes from baseline in PEC score at each time point assessed up to two hours following the initial dose. In Study 1, the decrease in agitation with IGALMI, compared to placebo, was statistically significant beginning at 20 minutes following dosing with the 180 mcg dose and 30 minutes after the 120 mcg dose. In Study 2, the decrease in agitation with IGALMI, compared to placebo, was statistically significant beginning at 20 minutes after treatment with both 120 mcg and 180 mcg doses.

Figure 1: Mean Change from Baseline in PEC Score Through Two Hours after a Single Dose in Agitated Patients with Schizophrenia (Study 1)

Figure 2: Mean Change from Baseline in PEC Score Through Two Hours after a Single Dose in Agitated Patients with Bipolar I or II Disorder (Study 2)

16 HOW SUPPLIED/STORAGE AND HANDLING

How Supplied

IGALMI (dexmedetomidine) sublingual film is supplied as a blue rectangular sublingual film, containing on its surface two darker blue spots in dose strengths of 120 mcg and 180 mcg and is packaged as individual films in heat-sealed foil pouches in 10-count and 30-count films per carton. The NDC number for each packaging configuration is:

- 120 mcg 10-count NDC # 81092-1120-1
- 120 mcg 30-count NDC # 81092-1120-3
- 180 mcg 10-count NDC # 81092-1180-1
- 180 mcg 30-count NDC # 81092-1180-3

Storage and Handling

Store at controlled room temperature, 20°C to 25°C (68°F to 77°F). Excursions permitted from 15°C to 30°C (59°F to 86°F). See USP Controlled Room Temperature.

Keep IGALMI in the foil pouch until ready to administer.

17 PATIENT COUNSELING INFORMATION

Administration Information

Advise patients to place IGALMI under the tongue, close to the base of the tongue, on the left or right side (sublingual) or behind the lower lip (buccal).

Advise patients not to chew or swallow IGALMI. Also, advise patients not to eat or drink for at least 15 minutes after sublingual administration, or at least 1 hour after buccal administration [see Dosage and Administration (2.3)].

Hypotension, Orthostatic Hypotension, and Bradycardia

Advise patients that IGALMI can cause dose-dependent hypotension, orthostatic hypotension, and bradycardia. Inform patients to remain sitting or lying down after receiving IGALMI and to inform the healthcare provider if they have any symptoms of hypotension or bradycardia [see Warnings and Precautions (5.1)].

QT Interval Prolongation

Inform patients to consult their physician immediately if they feel faint or have heart palpitations [see Warnings and Precautions (5.2)].

Somnolence

Advise patients that IGALMI can cause somnolence and may impair the ability to perform tasks that require complex motor and mental skills. Advise patients that they should avoid doing activities that require them to be alert, such as driving a car or operating machinery for at least eight hours after receiving IGALMI [see Warnings and Precautions (5.3)].

Lactation

Advise patients exposed to IGALMI to monitor breastfed infants for irritability [see Use in Specific Populations (8.2)].

Distributed by:
BioXcel Therapeutics, Inc.
555 Long Wharf Drive 12th Floor
New Haven, CT 06511

IGALMI is a registered trademark of BioXcel Therapeutics, Inc.
All other trademarks are the properties of their respective owners.
Copyright © 2022, BioXcel Therapeutics, Inc. All rights reserved.
MFG-0028v3.0

PRINCIPAL DISPLAY PANEL - 120 mcg Film Pouch Carton

Rx Only

Igalmi™
(dexmedetomidine) sublingual film

For sublingual or buccal use
Keep IGALMI in pouch until administration
Do not chew or swallow the film

120 mcg

10 pouches
Each containing
1 film

NDC 81092-1120-1

PRINCIPAL DISPLAY PANEL - 180 mcg Film Pouch Carton

Rx Only

Igalmi™
(dexmedetomidine) sublingual film

For sublingual or buccal use
Keep IGALMI in pouch until administration
Do not chew or swallow the film

180 mcg

10 pouches
Each containing
1 film

NDC 81092-1180-1